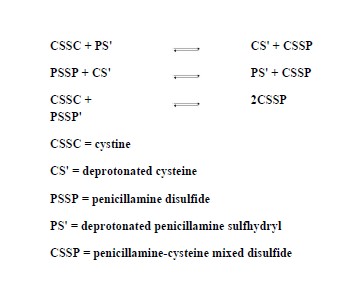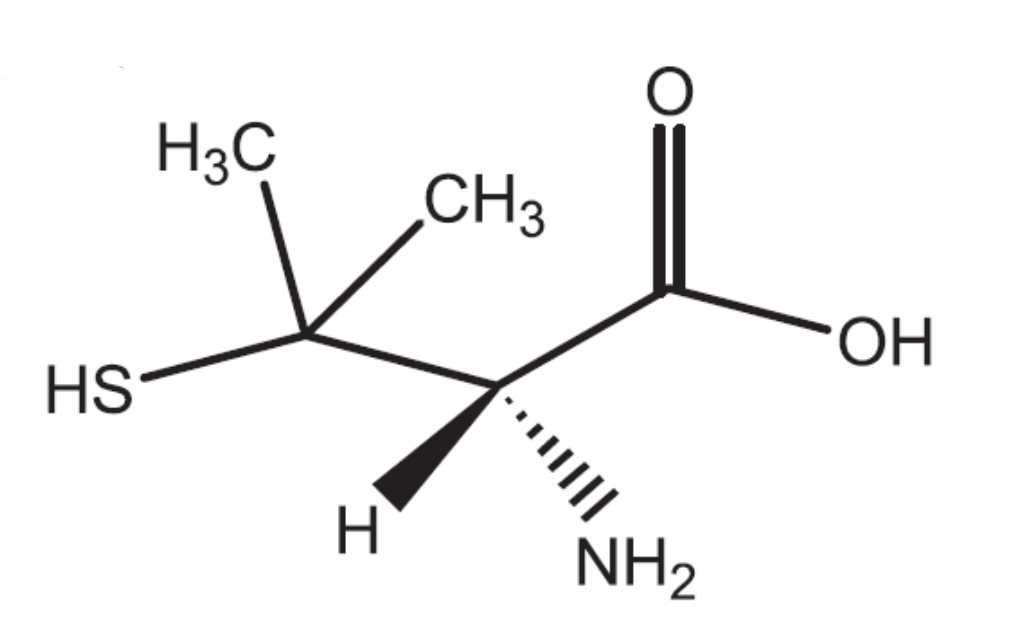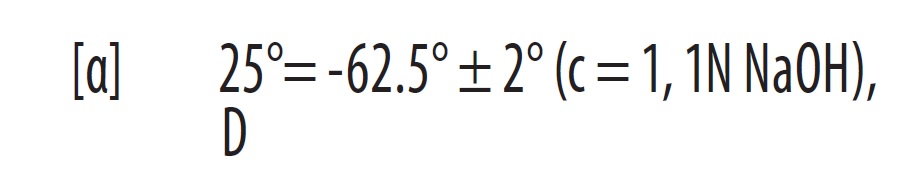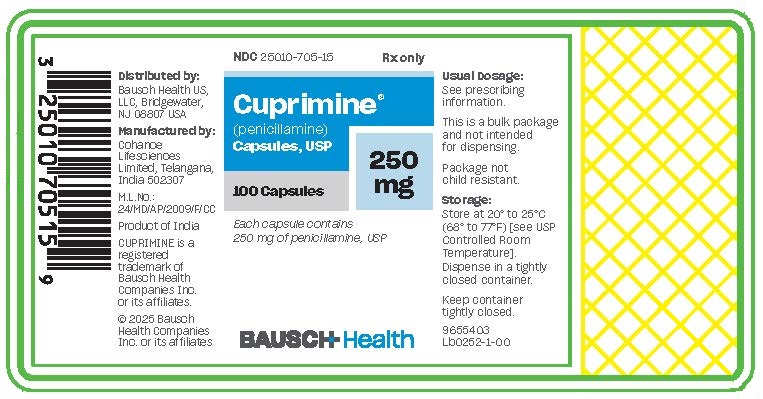 DRUG LABEL: Cuprimine
NDC: 25010-705 | Form: CAPSULE
Manufacturer: Bausch Health US, LLC
Category: prescription | Type: HUMAN PRESCRIPTION DRUG LABEL
Date: 20260126

ACTIVE INGREDIENTS: PENICILLAMINE 250 mg/1 1
INACTIVE INGREDIENTS: D&C YELLOW NO. 10; GELATIN, UNSPECIFIED; MAGNESIUM STEARATE; TITANIUM DIOXIDE; LACTOSE MONOHYDRATE

Cuprimine®
(penicillamine)
Capsules, USP

BOXED WARNING

Physicians planning to use penicillamine should thoroughly familiarize themselves with its toxicity, special dosage considerations, and therapeutic benefits. Penicillamine should never be used casually. Each patient should remain constantly under the close supervision of the physician. Patients should be warned to report promptly any symptoms suggesting toxicity.

DESCRIPTION

Penicillamine, USP is a chelating agent used in the treatment of Wilson’s disease. It is also used to reduce cystine excretion in cystinuria and to treat patients with severe, active rheumatoid arthritis unresponsive to conventional therapy (see INDICATIONS). It is 3-mercapto-D-valine. It is a white, or practically white, crystalline powder, freely soluble in water, slightly soluble in alcohol, and insoluble in ether, acetone, benzene, and carbon tetrachloride. Although its configuration is D, it is levorotatory as usually measured:

calculated on a dried basis.

The empirical formula is C5H11NO2S, giving it a molecular weight of 149.21. The structural formula is:

It reacts readily with formaldehyde or acetone to form a thiazolidine-carboxylic acid. CUPRIMINE (penicillamine) Capsules, USP for oral administration contain 250 mg of penicillamine. Each capsule contains the following inactive ingredients: D&C Yellow No. 10, gelatin, lactose monohydrate, magnesium stearate, and titanium dioxide.

CLINICAL PHARMACOLOGY

Penicillamine is a chelating agent recommended for the removal of excess copper in patients with Wilson’s disease. From in vitro studies which indicate that one atom of copper combines with two molecules of penicillamine, it would appear that 1 g of penicillamine should be followed by the excretion of about 200 mg of copper; however, the actual amount excreted is about 1% of this.

Penicillamine also reduces excess cystine excretion in cystinuria. This is done, at least in part, by disulfide interchange between penicillamine and cystine, resulting in formation of penicillamine-cysteine disulfide, a substance that is much more soluble than cystine and is excreted readily.

Penicillamine interferes with the formation of cross-links between tropocollagen molecules and cleaves them when newly formed.

The mechanism of action of penicillamine in rheumatoid arthritis is unknown although it appears to suppress disease activity. Unlike cytotoxic immunosuppressants, penicillamine markedly lowers IgM rheumatoid factor but produces no significant depression in absolute levels of serum immunoglobulins. Also unlike cytotoxic immunosuppressants which act on both, penicillamine in vitro depresses T-cell activity but not B-cell activity.

In vitro, penicillamine dissociates macroglobulins (rheumatoid factor) although the relationship of the activity to its effect in rheumatoid arthritis is not known.

In rheumatoid arthritis, the onset of therapeutic response to CUPRIMINE may not be seen for 2 or 3 months. In those patients who respond, however, the first evidence of suppression of symptoms such as pain, tenderness, and swelling is generally apparent within 3 months. The optimum duration of therapy has not been determined. If remissions occur, they may last from months to years, but usually require continued treatment (see DOSAGE AND ADMINISTRATION).

In all patients receiving penicillamine, it is important that CUPRIMINE be given on an empty stomach, at least 1 hour before meals or 2 hours after meals, and at least 1 hour apart from any other drug, food, milk, antacid, zinc, or iron-containing preparation. This permits maximum absorption and reduces the likelihood of inactivation by metal binding in the gastrointestinal tract.

Pharmacokinetics

Penicillamine is absorbed rapidly but incompletely (40-70%) from the gastrointestinal tract, with wide inter-individual variations. Food, antacids, and iron reduce absorption of the drug. The peak plasma concentration of penicillamine occurs 1 to 3 hours after ingestion; it is approximately 1 to 2 mg/L after an oral dose of 250 mg. The drug appears in the plasma as free penicillamine, penicillamine disulfide, and penicillamine-cysteine disulfide. When prolonged treatment is stopped, there is a slow elimination phase lasting 4 to 6 days.

More than 80% of plasma penicillamine is bound to proteins, especially albumin and ceruloplasmin. The drug also binds to erythrocytes and macrophages. A small fraction of the dose is metabolized in the liver to S-methyl-D-penicillamine. Excretion is mainly renal, mainly as disulfides.

INDICATIONS

CUPRIMINE is indicated in the treatment of Wilson’s disease, cystinuria, and in patients with severe, active rheumatoid arthritis who have failed to respond to an adequate trial of conventional therapy. Available evidence suggests that CUPRIMINE is not of value in ankylosing spondylitis.

Wilson’s disease (hepatolenticular degeneration) occurs in individuals who have inherited an autosomal-recessive defect that leads to an accumulation of copper far in excess of metabolic requirements. The excess copper is deposited in several organs and tissues, and eventually produces pathological effects primarily in the liver, where damage progresses to postnecrotic cirrhosis, and in the brain, where degeneration is widespread. Copper is also deposited as characteristic, asymptomatic, golden-brown Kayser-Fleischer rings in the corneas of all patients with cerebral symptomatology and some patients who are either asymptomatic or manifest only hepatic symptomatology.

Two types of patients require treatment for Wilson’s disease: (1) the symptomatic, and (2) the asymptomatic in whom it can be assumed the disease will develop in the future if the patient is not treated.

The diagnosis, if suspected on the basis of family or individual history or physical examination, can be confirmed if the plasma copper-protein ceruloplasmin** is less than 20 mg/dL and either a quantitative determination in a liver biopsy specimen shows an abnormally high concentration of copper (greater than 250 mcg/g dry weight) or Kayser-Fleischer rings are present.

Treatment has two objectives:

(1) to minimize dietary intake of copper;

(2) to promote excretion and complex formation (i.e., detoxification) of excess tissue copper.

The first objective is attained by a daily diet that contains no more than 1 or 2 mg of copper. Such a diet should exclude, most importantly, chocolate, nuts, shellfish, mushrooms, liver, molasses, broccoli, and cereals and dietary supplements enriched with copper, and be composed to as great an extent as possible of foods with a low copper content. Distilled or demineralized water should be used if the patient’s drinking water contains more than 0.1 mg/L of copper.

For the second objective, a copper chelating agent is used.

In symptomatic patients, this treatment usually produces marked neurologic improvement, fading of Kayser-Fleischer rings, and gradual amelioration of hepatic dysfunction and psychic disturbances.

Clinical experience to date suggests that life is prolonged with the above regimen.

Noticeable improvement may not occur for 1 to 3 months. Occasionally, neurologic symptoms become worse during initiation of therapy with CUPRIMINE. Despite this, the drug should not be withdrawn. Temporary interruption carries an increased risk of developing a sensitivity reaction upon resumption of therapy, although it may result in clinical improvement of neurological symptoms (see WARNINGS). If the neurological symptoms and signs continue to worsen for a month after the initiation of CUPRIMINE therapy, several short courses of treatment with 2,3 - dimercaprol (BAL) while continuing CUPRIMINE may be considered.

Treatment of asymptomatic patients has been carried out for over 30 years. Symptoms and signs of the disease appear to be prevented indefinitely if daily treatment with CUPRIMINE is continued.

Cystinuria

Cystinuria is characterized by excessive urinary excretion of the dibasic amino acids, arginine, lysine, ornithine, and cystine, and the mixed disulfide of cysteine and homocysteine. The metabolic defect that leads to cystinuria is inherited as an autosomal-recessive trait. Metabolism of the affected amino acids is influenced by at least two abnormal factors: (1) defective gastrointestinal absorption and (2) renal tubular dysfunction.

Arginine, lysine, ornithine, and cysteine are soluble substances, readily excreted. There is no apparent pathology connected with their excretion in excessive quantities.

Cystine, however, is so slightly soluble at the usual range of urinary pH that it is not excreted readily, and so crystallizes and forms stones in the urinary tract. Stone formation is the only known pathology in cystinuria.

Normal daily output of cystine is 40 to 80 mg. In cystinuria, output is greatly increased and may exceed 1 g/day. At 500 to 600 mg/day, stone formation is almost certain. When it is more than 300 mg/day, treatment is indicated.

Conventional treatment is directed at keeping urinary cystine diluted enough to prevent stone formation, keeping the urine alkaline enough to dissolve as much cystine as possible, and minimizing cystine production by a diet low in methionine (the major dietary precursor of cystine). Patients must drink enough fluid to keep urine-specific gravity below 1.010, take enough alkali to keep urinary pH at 7.5 to 8, and maintain a diet low in methionine. This diet is not recommended in growing children and probably is contraindicated in pregnancy because of its low protein content (see PRECAUTIONS).

When these measures are inadequate to control recurrent stone formation, CUPRIMINE may be used as additional therapy, and when patients refuse to adhere to conventional treatment, CUPRIMINE may be a useful substitute. It is capable of keeping cystine excretion to near normal values, thereby hindering stone formation and the serious consequences of pyelonephritis and impaired renal function that develop in some patients. Bartter and colleagues depict the process by which penicillamine interacts with cystine to form penicillamine-cysteine mixed disulfide as:

In this process, it is assumed that the deprotonated form of penicillamine, PS’, is the active factor in bringing about the disulfide interchange.

Rheumatoid Arthritis

Because CUPRIMINE can cause severe adverse reactions, its use in rheumatoid arthritis should be restricted to patients who have severe, active disease and who have failed to respond to an adequate trial of conventional therapy. Even then, benefit-to-risk ratio should be carefully considered. Other measures, such as rest, physiotherapy, salicylates, and corticosteroids, should be used, when indicated, in conjunction with CUPRIMINE (see PRECAUTIONS).

CONTRAINDICATIONS

Except for the treatment of Wilson’s disease or certain patients with cystinuria, use of penicillamine during pregnancy is contraindicated (see WARNINGS).

Although breast milk studies have not been reported in animals or humans, mothers on therapy with penicillamine should not nurse their infants.

Patients with a history of penicillamine-related aplastic anemia or agranulocytosis should not be restarted on penicillamine (see WARNINGS and ADVERSE REACTIONS).

Because of its potential for causing renal damage, penicillamine should not be administered to rheumatoid arthritis patients with a history or other evidence of renal insufficiency.

WARNINGS

The use of penicillamine has been associated with fatalities due to certain diseases such as aplastic anemia, agranulocytosis, thrombocytopenia, Goodpasture’s syndrome, and myasthenia gravis.

Because of the potential for serious hematological and renal adverse reactions to occur at any time, routine urinalysis, white and differential blood cell count, hemoglobin determination, and direct platelet count must be done twice weekly, together with monitoring of the patient’s skin, lymph nodes, and body temperature, during the first month of therapy, every two weeks for the next 5 months, and monthly thereafter. Patients should be instructed to report promptly the development of signs and symptoms of granulocytopenia and/or thrombocytopenia such as fever, sore throat, chills, bruising, or bleeding. The above laboratory studies should then be promptly repeated.

Leukopenia and thrombocytopenia have been reported to occur in up to 5% of patients during penicillamine therapy. Leukopenia is of the granulocytic series and may or may not be associated with an increase in eosinophils. A confirmed reduction in White Blood Cells (WBC) below 3500/mm^3 mandates discontinuance of penicillamine therapy. Thrombocytopenia may be on an idiosyncratic basis, with decreased or absent megakaryocytes in the marrow, when it is part of an aplastic anemia. In other cases, the thrombocytopenia is presumably on an immune basis since the number of megakaryocytes in the marrow has been reported to be normal or sometimes increased. The development of a platelet count below 100,000/mm^3, even in the absence of clinical bleeding, requires at least temporary cessation of penicillamine therapy. A progressive fall in either platelet count or WBC count in three successive determinations, even though values are still within the normal range, likewise requires at least temporary cessation.

Proteinuria and/or hematuria may develop during therapy and may be warning signs of membranous glomerulopathy which can progress to a nephrotic syndrome. Close observation of these patients is essential. In some patients, the proteinuria disappears with continued therapy; in others, penicillamine must be discontinued. When a patient develops proteinuria or hematuria, the physician must ascertain whether it is a sign of drug-induced glomerulopathy or is unrelated to penicillamine.

Rheumatoid arthritis patients who develop moderate degrees of proteinuria may be continued cautiously on penicillamine therapy, provided that quantitative 24-hour urinary protein determinations are obtained at intervals of 1 to 2 weeks. Penicillamine dosage should not be increased under these circumstances. Proteinuria which exceeds 1 g/24 hours, or proteinuria which is progressively increasing, requires either discontinuance of the drug or a reduction in the dosage. In some patients, proteinuria has been reported to clear following reduction in dosage.

In rheumatoid arthritis patients, penicillamine should be discontinued if unexplained gross hematuria or persistent microscopic hematuria develops.

In patients with Wilson’s disease or cystinuria, the risks of continued penicillamine therapy in patients manifesting potentially serious urinary abnormalities must be weighed against the expected therapeutic benefits.

When penicillamine is used in cystinuria, an annual x-ray for renal stones is advised. Cystine stones form rapidly, sometimes in 6 months. Up to one year or more may be required for any urinary abnormalities to disappear after penicillamine has been discontinued.

Because of rare reports of intrahepatic cholestasis and toxic hepatitis, liver function tests are recommended every 6 months for the duration of therapy. In Wilson’s disease, these are recommended every 3 months, at least during the first year of treatment.

Goodpasture’s syndrome has occurred rarely. The development of abnormal urinary findings associated with hemoptysis and pulmonary infiltrates on x-ray requires immediate cessation of penicillamine.

Obliterative bronchiolitis has been reported rarely. The patient should be cautioned to report immediately pulmonary symptoms such as exertional dyspnea, unexplained cough, or wheezing. Pulmonary function studies should be considered at that time.

Onset of new neurological symptoms has been reported with CUPRIMINE (see ADVERSE REACTIONS). Occasionally, neurological symptoms become worse during initiation of therapy with CUPRIMINE (see INDICATIONS). Myasthenic syndrome sometimes progressing to myasthenia gravis has been reported. Ptosis and diplopia, with weakness of the extraocular muscles, are often early signs of myasthenia. In the majority of cases, symptoms of myasthenia have receded after withdrawal of penicillamine.

Most of the various forms of pemphigus have occurred during treatment with penicillamine. Pemphigus vulgaris and pemphigus foliaceus are reported most frequently, usually as a late complication of therapy. The seborrhea-like characteristics of pemphigus foliaceus may obscure an early diagnosis. When pemphigus is suspected, CUPRIMINE should be discontinued. Treatment has consisted of high doses of corticosteroids alone or, in some cases, concomitantly with an immunosuppressant. Treatment may be required for only a few weeks or months, but may need to be continued for more than a year.

Once instituted for Wilson’s disease or cystinuria, treatment with penicillamine should, as a rule, be continued on a daily basis. Interruptions for even a few days have been followed by sensitivity reactions after reinstitution of therapy.

Pregnancy

Penicillamine can cause fetal harm when administered to a pregnant woman. Penicillamine has been shown to be teratogenic in rats when given in doses six times higher than the highest dose recommended for human use. Skeletal defects, cleft palates, and fetal toxicity (resorptions) have been reported.

There are no controlled studies on the use of penicillamine in pregnant women. Although normal outcomes have been reported, characteristic congenital cutis laxa and associated birth defects have been reported in infants born of mothers who received therapy with penicillamine during pregnancy. Penicillamine should be used in women of childbearing potential only when the expected benefits outweigh the possible hazards. Women on therapy with penicillamine who are of childbearing potential should be apprised of this risk, advised to report promptly any missed menstrual periods or other indications of possible pregnancy, and followed closely for early recognition of pregnancy. If this drug is used during pregnancy, or if the patient becomes pregnant while taking this drug, the patient should be apprised of the potential hazard to the fetus.

Wilson’s Disease

Reported experience*** shows that continued treatment with penicillamine throughout pregnancy protects the mother against relapse of Wilson’s disease, and that discontinuation of penicillamine has deleterious effects on the mother, which may be fatal.

If penicillamine is administered during pregnancy to patients with Wilson’s disease, it is recommended that the daily dosage be limited to 750 mg. If cesarean section is planned, the daily dose should be reduced to 250 mg, but not lower, for the last 6 weeks of pregnancy and postoperatively until wound healing is complete.

Cystinuria

If possible, penicillamine should not be given during pregnancy to women with cystinuria (see CONTRAINDICATIONS). There are reports of women with cystinuria on therapy with penicillamine who gave birth to infants with generalized connective tissue defects who died following abdominal surgery. If stones continue to form in these patients, the benefits of therapy to the mother must be evaluated against the risk to the fetus.

Rheumatoid Arthritis

Penicillamine should not be administered to rheumatoid arthritis patients who are pregnant (see CONTRAINDICATIONS) and should be discontinued promptly in patients in whom pregnancy is suspected or diagnosed. There is a report that a woman with rheumatoid arthritis treated with less than 1 g/day of penicillamine during pregnancy gave birth (cesarean delivery) to an infant with growth retardation, flattened face with broad nasal bridge, low set ears, short neck with loose skin folds, and unusually lax body skin.

PRECAUTIONS

Some patients may experience drug fever, a marked febrile response to penicillamine, usually in the second to third week following initiation of therapy. Drug fever may sometimes be accompanied by a macular cutaneous eruption. In the case of drug fever in patients with Wilson’s disease or cystinuria, penicillamine should be temporarily discontinued until the reaction subsides. Then penicillamine should be reinstituted with a small dose that is gradually increased until the desired dosage is attained. Systemic steroid therapy may be necessary, and is usually helpful, in such patients in whom drug fever and rash develop several times.

In the case of drug fever in rheumatoid arthritis patients, because other treatments are available, penicillamine should be discontinued and another therapeutic alternative tried since experience indicates that the febrile reaction will recur in a very high percentage of patients upon readministration of penicillamine.

The skin and mucous membranes should be observed for allergic reactions. Early and late rashes have occurred. Early rash occurs during the first few months of treatment and is more common. It is usually a generalized pruritic, erythematous, maculopapular, or morbilliform rash and resembles the allergic rash seen with other drugs. Early rash usually disappears within days after stopping penicillamine and seldom recurs when the drug is restarted at a lower dosage. Pruritus and early rash may often be controlled by the concomitant administration of antihistamines.

Less commonly, a late rash may be seen, usually after 6 months or more of treatment, which requires discontinuation of penicillamine. It is usually on the trunk, is accompanied by intense pruritus, and is usually unresponsive to topical corticosteroid therapy. Late rash may take weeks to disappear after penicillamine is stopped and usually recurs if the drug is restarted.

The appearance of a drug eruption accompanied by fever, arthralgia, lymphadenopathy, or other allergic manifestations usually requires discontinuation of penicillamine.

Certain patients will develop a positive antinuclear antibody (ANA) test and some of these may show a lupus erythematosus-like syndrome similar to drug-induced lupus associated with other drugs. The lupus erythematosus-like syndrome is not associated with hypocomplementemia and may be present without nephropathy. The development of a positive ANA test does not mandate discontinuance of the drug; however, the physician should be alerted to the possibility that a lupus erythematosus-like syndrome may develop in the future.

Some patients may develop oral ulcerations which in some cases have the appearance of aphthous stomatitis. The stomatitis usually recurs on rechallenge but often clears on a lower dosage. Although rare, cheilosis, glossitis, and gingivostomatitis have also been reported. These oral lesions are frequently dose-related and may preclude further increase in penicillamine dosage or require discontinuation of the drug.

Hypogeusia (a blunting or diminution in taste perception) has occurred in some patients. This may last 2 to 3 months or more and may develop into a total loss of taste; however, it is usually self-limited despite continued penicillamine treatment. Such taste impairment is rare in patients with Wilson’s disease.

Penicillamine should not be used in patients who are receiving concurrently gold therapy, antimalarial or cytotoxic drugs, oxyphenbutazone or phenylbutazone because these drugs are also associated with similar serious hematologic and renal adverse reactions.

Patients who have had gold salt therapy discontinued due to a major toxic reaction may be at greater risk of serious adverse reactions with penicillamine but not necessarily of the same type.

Patients who are allergic to penicillin may theoretically have cross-sensitivity to penicillamine. The possibility of reactions from contamination of penicillamine by trace amounts of penicillin has been eliminated now that penicillamine is being produced synthetically rather than as a degradation product of penicillin.

Patients with Wilson’s disease or cystinuria should be given 25 mg/day of pyridoxine during therapy, since penicillamine increases the requirement for this vitamin. Patients also may receive benefit from a multivitamin preparation, although there is no evidence that deficiency of any vitamin other than pyridoxine is associated with penicillamine. In Wilson’s disease, multivitamin preparations must be copper-free.

Rheumatoid arthritis patients whose nutrition is impaired should also be given a daily supplement of pyridoxine. Mineral supplements should not be given, since they may block the response to penicillamine. Iron deficiency may develop, especially in pediatric patients and in menstruating women. In Wilson’s disease, this may be a result of adding the effects of the low copper diet, which is probably also low in iron, and the penicillamine to the effects of blood loss or growth. In cystinuria, a low methionine diet may contribute to iron deficiency, since it is necessarily low in protein. If necessary, iron may be given in short courses, but a period of 2 hours should elapse between administration of penicillamine and iron, since orally administered iron has been shown to reduce the effects of penicillamine.

Penicillamine causes an increase in the amount of soluble collagen. In the rat, this results in inhibition of normal healing and also a decrease in tensile strength of intact skin. In man, this may be the cause of increased skin friability at sites especially subject to pressure or trauma, such as shoulders, elbows, knees, toes, and buttocks. Extravasations of blood may occur and may appear as purpuric areas, with external bleeding if the skin is broken, or as vesicles containing dark blood. Neither type is progressive. There is no apparent association with bleeding elsewhere in the body and no associated coagulation defect has been found. Therapy with penicillamine may be continued in the presence of these lesions. They may not recur if dosage is reduced. Other reported effects probably due to the action of penicillamine on collagen are excessive wrinkling of the skin and development of small, white papules at venipuncture and surgical sites.

The effects of penicillamine on collagen and elastin make it advisable to consider a reduction in dosage to 250 mg/day, when surgery is contemplated. Reinstitution of full therapy should be delayed until wound healing is complete.

Carcinogenesis, Mutagenesis, Impairment of Fertility

Long-term animal carcinogenicity studies have not been done with penicillamine. There is a report that five of ten autoimmune disease-prone New Zealand black (NZB) hybrid mice developed lymphocytic leukemia after 6 months’ intraperitoneal treatment with a dose of 400 mg/kg penicillamine 5 days per week.

Penicillamine is directly mutagenic to S. typhimurium strain TA92 in the Ames test; mutagenicity is enhanced by kidney postmitochondrial subcellular fraction 9. Penicillamine does not induce gene mutations in Chinese hamster V79 cells.

Penicillamine induces sister-chromatid exchanges and chromosome aberrations in cultivated mammalian cells. No studies on the effect of penicillamine on fertility are available.

PREGNANCY

Pregnancy

(see WARNINGS, Pregnancy)

Nursing Mothers

See CONTRAINDICATIONS.

Pediatric Use

The efficacy of CUPRIMINE in juvenile rheumatoid arthritis has not been established.

Geriatric Use

Clinical studies of CUPRIMINE are limited in subjects aged 65 and over; they did not include sufficient numbers of elderly subjects aged 65 and over to adequately determine whether they respond differently from younger subjects. Review of reported clinical trials with penicillamine in the elderly suggest greater risk than in younger patients for overall skin rash and abnormality of taste. In general, dose selection for an elderly patient should be cautious, starting at the low end of the dosing range, reflecting the greater frequency of decreased hepatic, renal, or cardiac function, and of concomitant disease or other drugs.

This drug is known to be substantially excreted by the kidney, and the risk of toxic reactions to this drug may be greater in patients with impaired renal function. Because elderly patients are more likely to have decreased renal function, care should be taken in dose selection and careful monitoring of renal function is recommended.

ADVERSE REACTIONS

Penicillamine is a drug with a high incidence of untoward reactions, some of which are potentially fatal. Therefore, it is mandatory that patients receiving penicillamine therapy remain under close medical supervision throughout the period of drug administration (see WARNINGS and PRECAUTIONS).

Reported incidences (%) for the most commonly occurring adverse reactions in rheumatoid arthritis patients are noted, based on 17 representative clinical trials reported in the literature (1270 patients).

Allergic

Generalized pruritus, early and late rashes (5%), pemphigus (see WARNINGS), and drug eruptions, which may be accompanied by fever, arthralgia, or lymphadenopathy have occurred (see WARNINGS and PRECAUTIONS). Some patients may show a lupus erythematosus-like syndrome similar to drug-induced lupus produced by other pharmacological agents (see PRECAUTIONS).

Urticaria and exfoliative dermatitis have occurred.

Thyroiditis has been reported; hypoglycemia in association with anti-insulin antibodies has been reported. These reactions are extremely rare.

Some patients may develop a migratory polyarthralgia, often with objective synovitis (see DOSAGE AND ADMINISTRATION).

Gastrointestinal

Anorexia, epigastric pain, nausea, vomiting, or occasional diarrhea may occur (17%).

Isolated cases of reactivated peptic ulcer have occurred, as have hepatic dysfunction including hepatic failure and pancreatitis. Intrahepatic cholestasis and toxic hepatitis have been reported rarely. There have been a few reports of increased serum alkaline phosphatase, lactic dehydrogenase, and positive cephalin flocculation and thymol turbidity tests.

Some patients may report a blunting, diminution, or total loss of taste perception (12%) or may develop oral ulcerations. Although rare, cheilosis, glossitis, and gingivostomatitis have been reported (see PRECAUTIONS).

Gastrointestinal side effects are usually reversible following cessation of therapy.

Hematological

Penicillamine can cause bone marrow depression (see WARNINGS). Leukopenia (2%) and thrombocytopenia (4%) also have occurred. Fatalities have been reported as a result of thrombocytopenia, agranulocytosis, aplastic anemia, and sideroblastic anemia.

Thrombotic thrombocytopenic purpura, hemolytic anemia, red cell aplasia, monocytosis, leukocytosis, eosinophilia, and thrombocytosis have also been reported.

Renal

Patients on penicillamine therapy may develop proteinuria (6%) and/or hematuria which, in some, may progress to the development of the nephrotic syndrome as a result of an immune complex membranous glomerulopathy (see WARNINGS). Renal failure has been reported.

Central Nervous System

Tinnitus, optic neuritis, and peripheral sensory and motor neuropathies (including polyradiculoneuropathy, i.e., Guillain-Barré syndrome) have been reported. Muscular weakness may or may not occur with the peripheral neuropathies. Visual and psychic disturbances; mental disorders; and agitation and anxiety have been reported.

Neuromuscular

Myasthenia gravis (see WARNINGS); dystonia.

Other

Adverse reactions that have been reported rarely include thrombophlebitis; hyperpyrexia (see PRECAUTIONS); falling hair or alopecia; lichen planus; polymyositis; dermatomyositis; mammary hyperplasia; elastosis perforans serpiginosa; toxic epidermal necrolysis; anetoderma (cutaneous macular atrophy); and Goodpasture’s syndrome, a severe and ultimately fatal glomerulonephritis associated with intra-alveolar hemorrhage (see WARNINGS). Vasculitis, including fatal renal vasculitis, has also been reported. Allergic alveolitis, obliterative bronchiolitis, interstitial pneumonitis, and pulmonary fibrosis have been reported in patients with severe rheumatoid arthritis, some of whom were receiving penicillamine. Bronchial asthma also has been reported.

Increased skin friability; excessive wrinkling of skin; and development of small white papules at venipuncture and surgical sites have been reported (see PRECAUTIONS); yellow nail syndrome.

The chelating action of the drug may cause increased excretion of other heavy metals such as zinc, mercury, and lead.

There have been reports associating penicillamine with leukemia. However, circumstances involved in these reports are such that a cause and effect relationship to the drug has not been established.

To report SUSPECTED ADVERSE REACTIONS, contact Bausch Health US, LLC at 1-800-321-4576 or FDA at 1-800-FDA-1088 or www.fda.gov/medwatch.

DOSAGE AND ADMINISTRATION

In all patients receiving penicillamine, it is important that CUPRIMINE be given on an empty stomach, at least one hour before meals or two hours after meals, and at least one hour apart from any other drug, food, or milk. Because penicillamine increases the requirement for pyridoxine, patients may require a daily supplement of pyridoxine (see PRECAUTIONS).

Wilson’s Disease

Optimal dosage can be determined by measurement of urinary copper excretion and the determination of free copper in the serum. The urine must be collected in copper-free glassware, and should be quantitatively analyzed for copper before and soon after initiation of therapy with CUPRIMINE.

Determination of 24-hour urinary copper excretion is of greatest value in the first week of therapy with penicillamine. In the absence of any drug reaction, a dose between 0.75 and 1.5 g that results in an initial 24-hour cupriuresis of over 2 mg should be continued for about 3 months, by which time the most reliable method of monitoring maintenance treatment is the determination of free copper in the serum. This equals the difference between quantitatively determined total copper and ceruloplasmin copper. Adequately treated patients will usually have less than 10 mcg free copper/dL of serum. It is seldom necessary to exceed a dosage of 2 g/day. If the patient is intolerant to therapy with CUPRIMINE, alternative treatment is trientine hydrochloride.

In patients who cannot tolerate as much as 1 g/day initially, initiating dosage with 250 mg/day and increasing gradually to the requisite amount, gives closer control of the effects of the drug and may help to reduce the incidence of adverse reactions.

Cystinuria

It is recommended that CUPRIMINE be used along with conventional therapy. By reducing urinary cystine, it decreases crystalluria and stone formation. In some instances, it has been reported to decrease the size of, and even to dissolve, stones already formed.

The usual dosage of CUPRIMINE in the treatment of cystinuria is 2 g/day for adults, with a range of 1 to 4 g/day. For pediatric patients, dosage can be based on 30 mg/kg/day. The total daily amount should be divided into four doses. If four equal doses are not feasible, give the larger portion at bedtime. If adverse reactions necessitate a reduction in dosage, it is important to retain the bedtime dose.

Initiating dosage with 250 mg/day, and increasing gradually to the requisite amount, gives closer control of the effects of the drug and may help to reduce the incidence of adverse reactions.

In addition to taking CUPRIMINE, patients should drink copiously. It is especially important to drink about a pint of fluid at bedtime and another pint once during the night when urine is more concentrated and more acid than during the day. The greater the fluid intake, the lower the required dosage of CUPRIMINE.

Dosage must be individualized to an amount that limits cystine excretion to 100 to 200 mg/day in those with no history of stones, and below 100 mg/day in those who have had stone formation and/or pain. Thus, in determining dosage, the inherent tubular defect, the patient’s size, age, and rate of growth, and his diet and water intake all must be taken into consideration.

The standard nitroprusside cyanide test has been reported useful as a qualitative measure of the effective dose:† Add 2 mL of freshly prepared 5% sodium cyanide to 5 mL of a 24-hour aliquot of protein-free urine and let stand 10 minutes. Add five drops of freshly prepared 5% sodium nitroprusside and mix. Cystine will turn the mixture magenta. If the result is negative, it can be assumed that cystine excretion is less than 100 mg/g creatinine.

Although penicillamine is rarely excreted unchanged, it also will turn the mixture magenta. If there is any question as to which substance is causing the reaction, a ferric chloride test can be done to eliminate doubt: Add 3% ferric chloride dropwise to the urine. Penicillamine will turn the urine an immediate and quickly fading blue. Cystine will not produce any change in appearance.

Rheumatoid Arthritis

The principal rule of treatment with CUPRIMINE in rheumatoid arthritis is patience. The onset of therapeutic response is typically delayed. Two or three months may be required before the first evidence of a clinical response is noted (see CLINICAL PHARMACOLOGY).

When treatment with CUPRIMINE has been interrupted because of adverse reactions or other reasons, the drug should be reintroduced cautiously by starting with a lower dosage and increasing slowly.

Initial Therapy — The currently recommended dosage regimen in rheumatoid arthritis begins with a single daily dose of 125 mg or 250 mg, which is thereafter increased at 1- to 3-month intervals, by 125 or 250 mg/day, as patient response and tolerance indicate. If a satisfactory remission of symptoms is achieved, the dose associated with the remission should be continued (see DOSAGE AND ADMINISTRATION, Rheumatoid Arthritis, Maintenance Therapy). If there is no improvement and there are no signs of potentially serious toxicity after 2 to 3 months of treatment with doses of 500 to 750 mg/day, increases of 250 mg/day at 2- to 3-month intervals may be continued until a satisfactory remission occurs (see DOSAGE AND ADMINISTRATION, Rheumatoid Arthritis, Maintenance Therapy) or signs of toxicity develop (see WARNINGS and PRECAUTIONS). If there is no discernible improvement after three to four months of treatment with 1000 to 1500 mg of penicillamine/day, it may be assumed the patient will not respond and CUPRIMINE should be discontinued.

Maintenance Therapy — The maintenance dosage of CUPRIMINE must be individualized, and may require adjustment during the course of treatment. Many patients respond satisfactorily to a dosage within the 500 to 750 mg/day range. Some need less.

Changes in maintenance dosage levels may not be reflected clinically or in the erythrocyte sedimentation rate for 2 to 3 months after each dosage adjustment.

Some patients will subsequently require an increase in the maintenance dosage to achieve maximal disease suppression. In those patients who do respond, but who evidence incomplete suppression of their disease after the first 6 to 9 months of treatment, the daily dosage of CUPRIMINE may be increased by 125 or 250 mg/day at 3-month intervals. It is unusual in current practice to employ a dosage in excess of 1 g/day, but up to 1.5 g/day has sometimes been required.

Managementof Exacerbations — During the course of treatment some patients may experience an exacerbation of disease activity following an initial good response. These may be self-limited and can subside within 12 weeks. They are usually controlled by the addition of nonsteroidal anti-inflammatory drugs, and only if the patient has demonstrated a true “escape” phenomenon (as evidenced by failure of the flare to subside within this time period) should an increase in the maintenance dose ordinarily be considered.

In the rheumatoid patient, migratory polyarthralgia due to penicillamine is extremely difficult to differentiate from an exacerbation of rheumatoid arthritis. Discontinuance or a substantial reduction in dosage of CUPRIMINE for up to several weeks will usually determine which of these processes is responsible for the arthralgia.

Duration of Therapy — The optimum duration of therapy with CUPRIMINE in rheumatoid arthritis has not been determined. If the patient has been in remission for 6 months or more, a gradual, stepwise dosage reduction in decrements of 125 mg or 250 mg/day at approximately 3-month intervals may be attempted.

Concomitant Drug Therapy — CUPRIMINE should not be used in patients who are receiving gold therapy, antimalarial or cytotoxic drugs, oxyphenbutazone, or phenylbutazone (see PRECAUTIONS). Other measures, such as salicylates, other nonsteroidal anti-inflammatory drugs, or systemic corticosteroids, may be continued when penicillamine is initiated. After improvement commences, analgesic and anti-inflammatory drugs may be slowly discontinued as symptoms permit. Steroid withdrawal must be done gradually, and many months of treatment with CUPRIMINE may be required before steroids can be completely eliminated.

Dosage Frequency — Based on clinical experience, dosages up to 500 mg/day can be given as a single daily dose. Dosages in excess of 500 mg/day should be administered in divided doses.

HOW SUPPLIED

CUPRIMINE Capsules, USP 250 mg, are pale yellow to ivory opaque hard gelatin capsules imprinted with “ATON 705” on the cap and “CUPRIMINE” on the body. They are supplied as follows:

NDC 25010-705-15 in bottles of 100

Storage

Store at 20° to 25°C (68° to 77°F) [see USP Controlled Room Temperature]. Dispense in a tightly closed container. Keep container tightly closed.

** For quantitative test for serum ceruloplasmin see: Morell, A.G.; Windsor, J.; Sternlieb, I.; Scheinberg, I.H.: Measurement of the concentration of ceruloplasmin in serum by determination of its oxidase activity, in “Laboratory Diagnosis of Liver Disease”, F.W. Sunderman; F.W. Sunderman, Jr. (eds.), St. Louis, Warren H. Green, Inc., 1968, pp. 193-195.

*** Scheinberg, I.H.; Sternlieb, I.: N. Engl. J. Med. 293: 1300-1302, Dec. 18, 1975.

† Lotz, M.; Potts, J.T. and Bartter, F.C.: Brit. Med. J. 2: 521, Aug. 28, 1965 (in Medical Memoranda).

Distributed by:
Bausch Health US, LLC
Bridgewater, NJ 08807 USA

Manufactured by:
Cohance Lifesciences Limited
Telangana, India 502307

M.L.No.: 24/MD/AP/2009/F/CC

CUPRIMINE is a registered trademark of Bausch Health Companies Inc. or its affiliates.

© 2025 Bausch Health Companies Inc. or its affiliates

Rev. 10/2025

9655603 Lb0252-2-00

PRINCIPAL DISPLAY PANEL - 100 mg Capsules Label

NDC25010-705-15

Rx only

Cuprimine®
(penicillamine)
Capsules, USP

250 mg
100 Capsules

Each capsule
contains 250 mg
of penicillamine, USP

BAUSCH Health